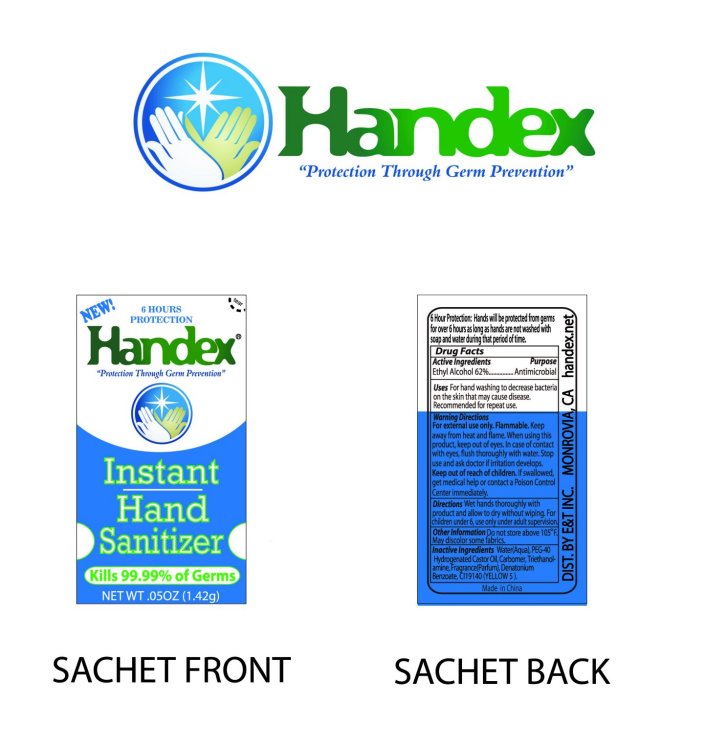 DRUG LABEL: Handex Instant Hand Sanitizer
NDC: 50756-100 | Form: GEL
Manufacturer: E T Inc.
Category: otc | Type: HUMAN OTC DRUG LABEL
Date: 20100302

ACTIVE INGREDIENTS: ALCOHOL 62 g/100 g
INACTIVE INGREDIENTS: WATER; POLYOXYL 40 HYDROGENATED CASTOR OIL; TROLAMINE; DENATONIUM BENZOATE; FD&C YELLOW NO. 5

Handex Instant Hand Sanitizer

Active Ingredients Purpose

Ethyl Alcohol 62 percent..................................................Antimicrobial

Uses

For Hand washing to decrease bacteria on the skin that may cause disease.

Recommended for repeat use.

6 hour protection: Hands will be protected from germs for over 6 hours as long

as hands are not washed with soap and water during that period of time.

WARNINGS

Warning Directions

For external use only. Flammable, keep away from heat and flame. When using this product keep out of eyes.

In case of contact with eyes, flush throughly with water. Stop use and ask a doctor if irritation develops.

Keep out of reach of Children.

If swallowed, get medical help or contact a Poison Control Center immediately.

Directions

Wet hands throughly with product and allow to dry without wiping.

For children under 6, use only under adult supervision.

Other Information

Do not store above 105 F.

May discolor some fabrics.

Inactive Ingredients

Water (Aqua), PEG-40 Hydrogenated Castor Oil, Carbomer, Triethanolamine, Fragrance (Parfum), Denatonium Benzoatem CI19140 (YELLOW 5).

DESCRIPTION

Made in China
Dist. By E and T Inc. Monrovia, Ca handex.net

PACKAGE LABEL

New!

Tear

6 Hour Protection

Handex
"Protection Through Germ Prevention"
Instant Hand Sanitizer
Kills 99.99 percent of germs
Net Wt .05oz (1.42g)